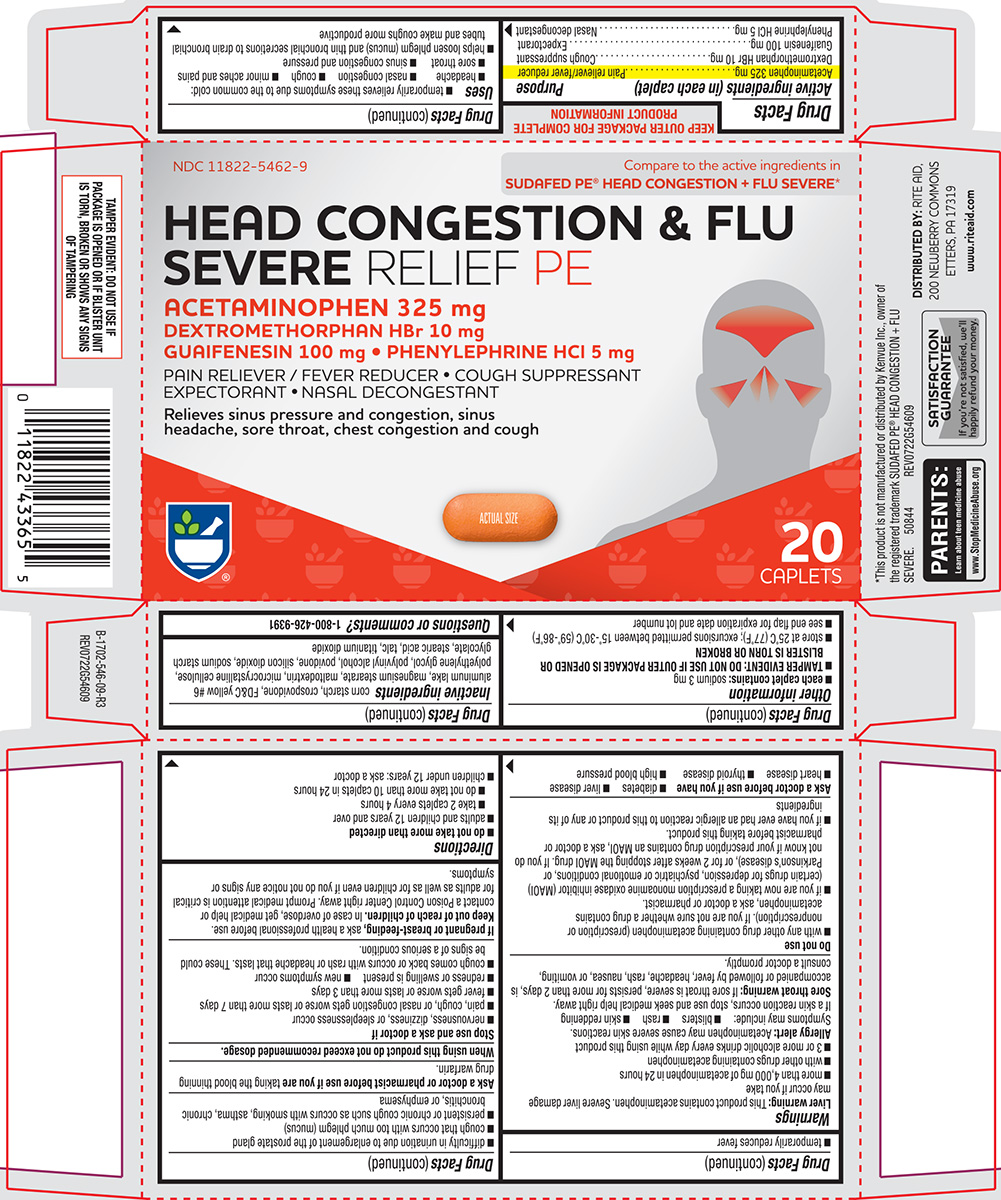 DRUG LABEL: Head Congestion and Flu Severe
NDC: 11822-5462 | Form: TABLET, FILM COATED
Manufacturer: Rite Aid Corporation
Category: otc | Type: HUMAN OTC DRUG LABEL
Date: 20260220

ACTIVE INGREDIENTS: ACETAMINOPHEN 325 mg/1 1; DEXTROMETHORPHAN HYDROBROMIDE 10 mg/1 1; GUAIFENESIN 100 mg/1 1; PHENYLEPHRINE HYDROCHLORIDE 5 mg/1 1
INACTIVE INGREDIENTS: STARCH, CORN; CROSPOVIDONE, UNSPECIFIED; FD&C YELLOW NO. 6 ALUMINUM LAKE; MAGNESIUM STEARATE; MALTODEXTRIN; MICROCRYSTALLINE CELLULOSE; POLYETHYLENE GLYCOL, UNSPECIFIED; POLYVINYL ALCOHOL, UNSPECIFIED; POVIDONE, UNSPECIFIED; SILICON DIOXIDE; SODIUM STARCH GLYCOLATE TYPE A POTATO; STEARIC ACID; TALC; TITANIUM DIOXIDE

Rite Aid 44-546-HCFS

Active ingredients (in each caplet)

Acetaminophen 325 mg
Dextromethorphan HBr 10 mg
Guaifenesin 100 mg
Phenylephrine HCl 5 mg

Purpose

Pain reliever/fever reducer
Cough suppressant
Expectorant
Nasal decongestant

Uses

- temporarily relieves these symptoms due to the common cold:
  - headache
  - nasal congestion
  - cough
  - sore throat
  - minor aches and pains
  - sinus congestion and pressure
- helps loosen phlegm (mucus) and thin bronchial secretions to drain bronchial tubes and make coughs more productive
- temporarily reduces fever

Warnings

Liver warning: This product contains acetaminophen. Severe liver damage may occur if you take

- more than 4,000 mg of acetaminophen in 24 hours
- with other drugs containing acetaminophen
- 3 or more alcoholic drinks every day while using this product

Allergy alert: Acetaminophen may cause severe skin reactions. Symptoms may include:

- blisters
- rash
- skin reddening

If a skin reaction occurs, stop use and seek medical help right away.

Sore throat warning: If sore throat is severe, persists for more than 2 days, is accompanied or followed by fever, headache, rash, nausea, or vomiting, consult a doctor promptly.

Do not use

- with any other drug containing acetaminophen (prescription or nonprescription). If you are not sure whether a drug contains acetaminophen, ask a doctor or pharmacist.
- if you are now taking a prescription monoamine oxidase inhibitor (MAOI) (certain drugs for depression, psychiatric or emotional conditions, or Parkinson’s disease), or for 2 weeks after stopping the MAOI drug. If you do not know if your prescription drug contains an MAOI, ask a doctor or pharmacist before taking this product.
- if you have ever had an allergic reaction to this product or any of its ingredients

Ask a doctor before use if you have

- diabetes
- liver disease
- heart disease
- thyroid disease
- high blood pressure
- difficulty in urination due to enlargement of the prostate gland
- cough that occurs with too much phlegm (mucus)
- persistent or chronic cough such as occurs with smoking, asthma, chronic bronchitis, or emphysema

Ask a doctor or pharmacist before use if you are

taking the blood thinning drug warfarin.

When using this product

do not exceed recommended dosage.

Stop use and ask a doctor if

- nervousness, dizziness, or sleeplessness occur
- pain, cough, or nasal congestion gets worse or lasts more than 7 days
- fever gets worse or lasts more than 3 days
- redness or swelling is present
- new symptoms occur
- cough comes back or occurs with rash or headache that lasts. These could be signs of a serious condition.

If pregnant or breast-feeding,

ask a health professional before use.

Keep out of reach of children.

In case of overdose, get medical help or contact a Poison Control Center right away. Prompt medical attention is critical for adults as well as for children even if you do not notice any signs or symptoms.

Directions

- do not take more than directed
- adults and children 12 years and over
  - take 2 caplets every 4 hours
  - do not take more than 10 caplets in 24 hours
- children under 12 years: ask a doctor

Other information

- each caplet contains: sodium 3 mg
- TAMPER EVIDENT: DO NOT USE IF OUTER PACKAGE IS OPENED OR BLISTER IS TORN OR BROKEN
- store at 25 ̊C (77 ̊F); excursions permitted between 15 ̊-30 ̊C (59 ̊-86 ̊F)
- see end flap for expiration date and lot number

Inactive ingredients

corn starch, crospovidone, FD&C yellow #6 aluminum lake, magnesium stearate, maltodextrin, microcrystalline cellulose, polyethylene glycol, polyvinyl alcohol, povidone, silicon dioxide, sodium starch glycolate, stearic acid, talc, titanium dioxide

Questions or comments?

1-800-426-9391

Principal display panel

NDC 11822-5462-9

Compare to the active ingredients in
SUDAFED PE® HEAD CONGESTION + FLU SEVERE*

HEAD CONGESTION & FLU SEVERE RELIEF PE

ACETAMINOPHEN 325 mg
DEXTROMETHORPHAN HBr 10 mg
GUAIFENESIN 100 mg • PHENYLEPHRINE HCl 5 mg

PAIN RELIEVER/ FEVER REDUCER • COUGH SUPPRESSANT
EXPECTORANT • NASAL DECONGESTANT

Relieves sinus pressure and congestion, sinus
headache, sore throat, chest congestion and cough

ACTUAL SIZE

20
CAPLETS

TAMPER EVIDENT: DO NOT USE IF
PACKAGE IS OPENED OR IF BLISTER UNIT
IS TORN, BROKEN OR SHOWS ANY SIGNS
OF TAMPERING

*This product is not manufactured or distributed by Kenvue Inc., owner of
the registered trademark SUDAFED PE® HEAD CONGESTION + FLU
SEVERE. 50844 REV0722G54609

SATISFACTION
GUARANTEE

If you're not satisfied, we'll
happily refund your money

DISTRIBUTED BY: RITE AID,
200 NEWBERRY COMMONS
ETTERS, PA 17319

www.riteaid.com

PARENTS:
Learn about teen medicine abuse
www.StopMedicineAbuse.org

Rite aid 44-546